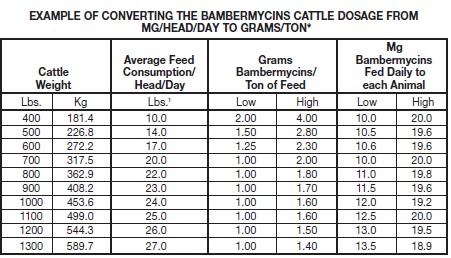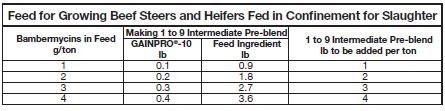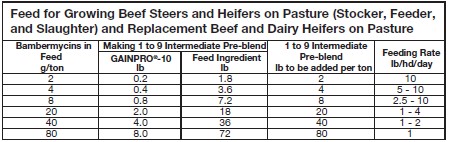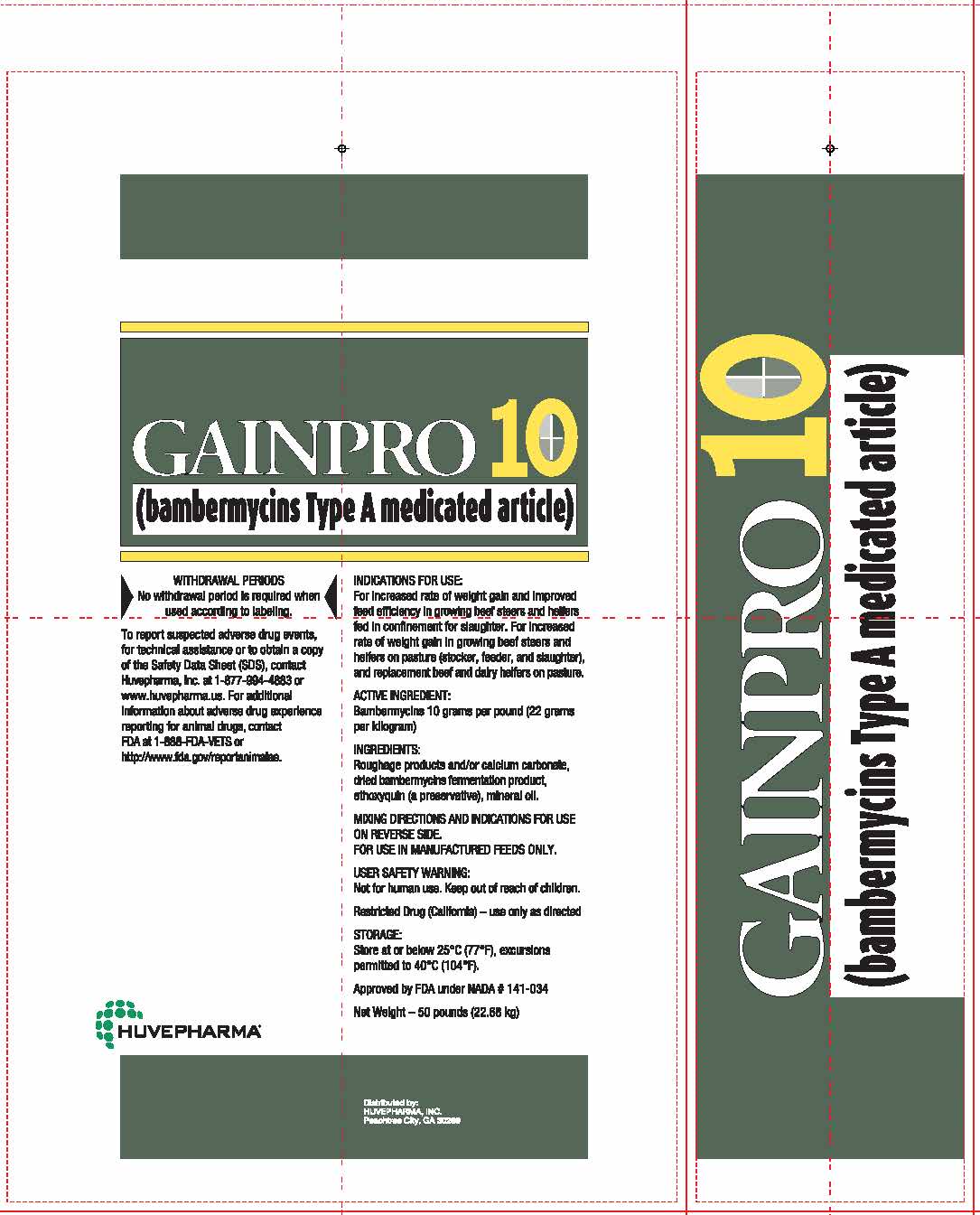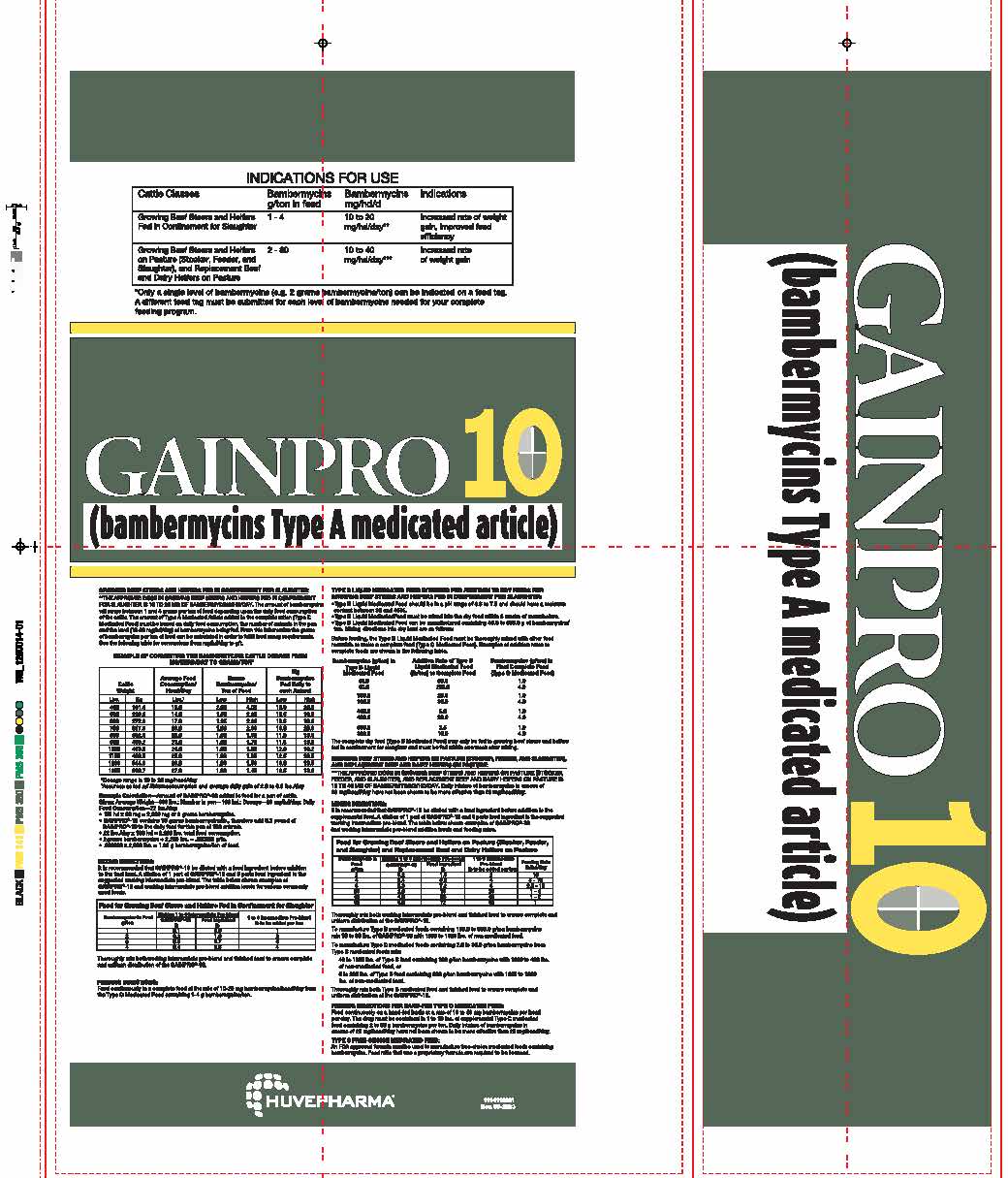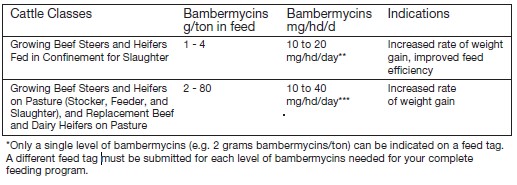 DRUG LABEL: Gainpro
NDC: 23243-2070 | Form: POWDER
Manufacturer: Huvepharma, Inc.
Category: animal | Type: OTC TYPE A MEDICATED ARTICLE ANIMAL DRUG LABEL
Date: 20240508

ACTIVE INGREDIENTS: BAMBERMYCINS 22 g/1 kg
INACTIVE INGREDIENTS: MINERAL OIL; ETHOXYQUIN

GAINPRO® 10
(bambermycins Type A medicated article)

RESIDUE WARNING

WITHDRAWAL PERIODS
No withdrawal period is required when
used according to labeling.

ADVERSE REACTIONS

To report suspected adverse drug events, for technical assistance or to obtain a copy
of the Safety Data Sheet (SDS), contact Huvepharma, Inc. at 1-877-994-4883 or
www.huvepharma.us. For additional information about adverse drug experience
reporting for animal drugs, contact FDA at 1-888-FDA-VETS or
http://www.fda.gov/reportanimalae.

INDICATIONS FOR USE:
For increased rate of weight gain and improved feed efficiency in growing beef steers and heifers
fed in confinement for slaughter. For increased rate of weight gain in growing beef steers and
heifers on pasture (stocker, feeder, and slaughter), and replacement beef and dairy heifers on pasture.

ACTIVE INGREDIENT:
Bambermycins 10 grams per pound (22 grams per kilogram)

INACTIVE INGREDIENT

INGREDIENTS:
Roughage products and/or calcium carbonate, dried bambermycins fermentation product,
ethoxyquin (a preservative), mineral oil.

VETERINARY INDICATIONS

MIXING DIRECTIONS AND INDICATIONS FOR USE ON REVERSE SIDE.
FOR USE IN MANUFACTURED FEEDS ONLY.

USER SAFETY WARNING:
Not for human use. Keep out of reach of children.

Restricted Drug (California) – use only as directed

STORAGE:
Store at or below 25°C (77°F), excursions permitted to 40°C (104°F).

Approved by FDA under NADA # 141-034

Net Weight – 50 pounds (22.68 kg)

HUVEPHARMA®

Distributed by:
HUVEPHARMA, INC.
Peachtree City, GA 30269

INDICATIONS AND USAGE

GROWING BEEF STEERS AND HEIFERS FED IN CONFINEMENT FOR SLAUGHTER:
**THE APPROVED DOSE IN GROWING BEEF STEERS AND HEIFERS FED IN CONFINEMENT
FOR SLAUGHTER IS 10 TO 20 MG OF BAMBERMYCINS/HD/DAY. The amount of bambermycins
will range between 1 and 4 grams per ton of feed depending upon the daily feed consumption
of the cattle. The amount of Type A Medicated Article added to the complete ration (Type C
Medicated Feed) must be based on daily feed consumption, the number of animals in the pen
and the level (10-20 mg/hd/day) of bambermycins being fed. From this information the grams
of bambermycins per ton of feed can be calculated in order to fulfill feed assay requirements.
See the following table for conversions from mg/hd/day to g/t.

*Dosage range is 10 to 20 mg/head/day
^1Assumes as fed ad libitum consumption and average daily gain of 2.0 to 3.0 lbs./day

Example Calculation—Amount of GAINPRO®-10 added to feed for a pen of cattle.
Given: Average Weight—800 lbs.; Number in pen—100 hd.; Dosage—20 mg/hd/day; Daily
Feed Consumption—22 lbs./day.
• 100 hd x 20 mg = 2,000 mg or 2 grams bambermycins.
• GAINPRO®-10 contains 10 grams bambermycins/lb., therefore add 0.2 pound of
GAINPRO®-10 to the daily feed for this pen of 100 animals.
• 22 lbs./day x 100 hd = 2,200 lbs. total feed consumption.
• 2 grams bambermycins ÷ 2,200 lbs. = .000909 g/lb.
• .000909 x 2,000 lbs. = 1.82 g bambermycins/ton of feed.

INDICATIONS AND USAGE

MIXING DIRECTIONS:
It is recommended that GAINPRO®-10 be diluted with a feed ingredient before addition
to the final feed. A dilution of 1 part of GAINPRO®-10 and 9 parts feed ingredient is the
suggested working intermediate pre-blend. The table below shows examples of
GAINPRO®-10 and working intermediate pre-blend addition levels for various commonly
used feeds.

Thoroughly mix both working intermediate pre-blend and finished feed to ensure complete
and uniform distribution of the GAINPRO®-10.

FEEDING DIRECTIONS:
Feed continuously in a complete feed at the rate of 10-20 mg bambermycins/head/day from
the Type C Medicated Feed containing 1-4 g bambermycins/ton.

TYPE B LIQUID MEDICATED FEED INTENDED FOR ADDITION TO DRY FEEDS FOR
GROWING BEEF STEERS AND HEIFERS FED IN CONFINEMENT FOR SLAUGHTER:
•Type B Liquid Medicated Feed should be in a pH range of 3.8 to 7.5 and should have a moisture
content between 30 and 45%.
•Type B Liquid Medicated Feed must be mixed into the dry feed within 8 weeks of manufacture.
•Type B Liquid Medicated Feed can be manufactured containing 40.0 to 800.0 g of bambermycins/
ton. Mixing directions into dry feed are as follows:
Before feeding, the Type B Liquid Medicated Feed must be thoroughly mixed with other feed
materials to make a complete feed (Type C Medicated Feed). Examples of addition rates to
complete feeds are shown in the following table.

Bambermycins (g/ton) in Type B Liquid Medicated Feed | Addition Rate of Type B Liquid Medicated Feed (lb/ton) to Complete Feed | Bambermycins (g/ton) in Final Complete Feed (Type C Medicated Feed)
40.0 | 50.0 | 1.0
40.0 | 200.0 | 4.0
100.0 | 20.0 | 1.0
100.0 | 80.0 | 4.0
400.0 | 5.0 | 1.0
400.0 | 20.0 | 4.0
800.0 | 2.5 | 1.0
800.0 | 10.0 | 4.0

The complete dry feed (Type C Medicated Feed) may only be fed to growing beef steers and heifers
fed in confinement for slaughter and must be fed within one week after mixing.

GROWING BEEF STEERS AND HEIFERS ON PASTURE (STOCKER, FEEDER, AND SLAUGHTER),
AND REPLACEMENT BEEF AND DAIRY HEIFERS ON PASTURE:
***THE APPROVED DOSE IN GROWING BEEF STEERS AND HEIFERS ON PASTURE (STOCKER,
FEEDER, AND SLAUGHTER), AND REPLACEMENT BEEF AND DAIRY HEIFERS ON PASTURE IS
10 TO 40 MG OF BAMBERMYCINS/HD/DAY. Daily intakes of bambermycins in excess of
20 mg/head/day have not been shown to be more effective than 20 mg/head/day.

MIXING DIRECTIONS:
It is recommended that GAINPRO®-10 be diluted with a feed ingredient before addition to the
supplemental feed. A dilution of 1 part of GAINPRO®-10 and 9 parts feed ingredient is the suggested
working intermediate pre-blend. The table below shows examples of GAINPRO®-10
and working intermediate pre-blend addition levels and feeding rates.

Thoroughly mix both working intermediate pre-blend and finished feed to ensure complete and
uniform distribution of the GAINPRO®-10.

To manufacture Type B medicated feeds containing 100.0 to 800.0 g/ton bambermycins
mix 10 to 80 lbs. of GAINPRO®-10 with 1990 to 1920 lbs. of non-medicated feed.

To manufacture Type C medicated feeds containing 2.0 to 80.0 g/ton bambermycins from
Type B medicated feeds mix:
40 to 1600 lbs. of Type B feed containing 100 g/ton bambermycins with 1960 to 400 lbs.
of non-medicated feed, or
5 to 200 lbs. of Type B feed containing 800 g/ton bambermycins with 1995 to 1800
lbs. of non-medicated feed.
Thoroughly mix both Type B medicated feed and finished feed to ensure complete and
uniform distribution of the GAINPRO®-10.

FEEDING DIRECTIONS FOR HAND-FED TYPE C MEDICATED FEED:
Feed continuously on a hand-fed basis at a rate of 10 to 40 mg bambermycins per head
per day. The drug must be contained in 1 to 10 lbs. of supplemental Type C medicated
feed containing 2 to 80 g bambermycins per ton. Daily intakes of bambermycins in
excess of 20 mg/head/day have not been shown to be more effective than 20 mg/head/day.

TYPE C FREE-CHOICE MEDICATED FEED:
An FDA approved formula must be used to manufacture free-choice medicated feeds containing
bambermycins. Feed mills that use a proprietary formula are required to be licensed.

HUVEPHARMA®